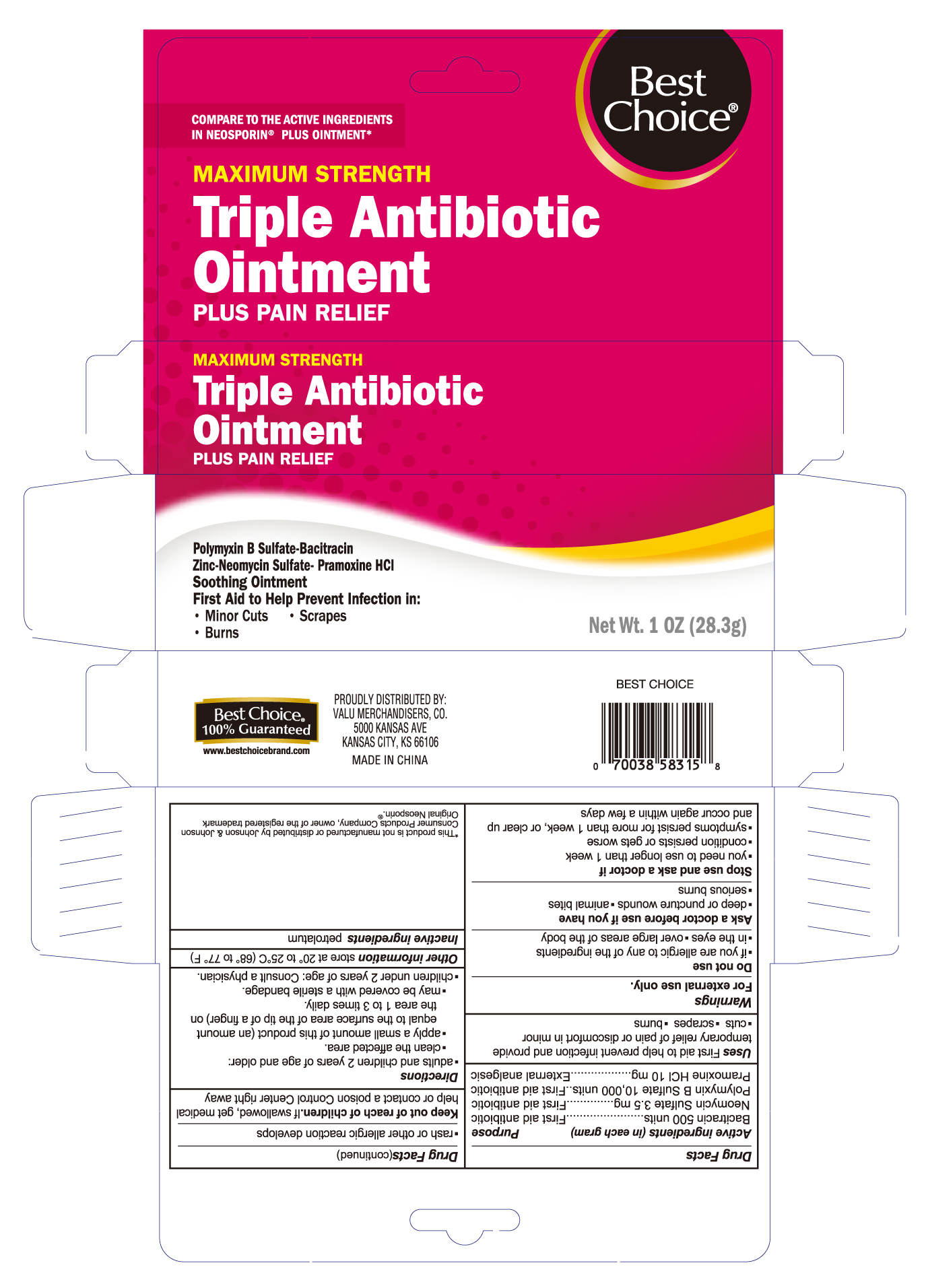 DRUG LABEL: Triple Antibiotic Plus Pain Relief
NDC: 63941-315 | Form: OINTMENT
Manufacturer: Valu Merchandisers, Co.
Category: otc | Type: HUMAN OTC DRUG LABEL
Date: 20230208

ACTIVE INGREDIENTS: BACITRACIN ZINC 500 [USP'U]/1 g; NEOMYCIN SULFATE 3.5 mg/1 g; POLYMYXIN B SULFATE 10000 [USP'U]/1 g; PRAMOXINE HYDROCHLORIDE 10 mg/1 g
INACTIVE INGREDIENTS: PETROLATUM

Best Choice Triple Antibiotic Ointment plus Pain Relief

Active ingredients (in each gram)

Bacitracin Zinc 500 units
Neomycin 3.5mg
Polymyxin B Sulfate 10,000 units
Pramoxine HCl 10mg

Purpose

First aid antibiotic

First aid antibiotic

First aid antibiotic

External analgesic

Uses

First aid to help prevent infection and provide temporary relief of pain or discomfort in minor

- cuts
- scrapes
- burns

Warnings

For external use only

Do not use

- if you are allergic to any of the ingredients
- in the eyes
- over large areas of the body

Ask a doctor before use if you have

- deep or puncture wounds
- animal bites
- serious burns

Stop use and ask a doctor if

- you need to use longer than 1 week
- condition persists or gets worse
- symptoms persists for more than 1 week, or clear up and occur again within a few days
- rash or other allergic reaction develops

Keep out of reach of children.

If swallowed, get medical help or contact a Poison Control Center right away.

Directions

- adults and children 2 years of age and older:
  - clean the affected area
  - apply a small amount of this product (an amount equal to the surface area of the tip of a finger) on the area 1 to 3 times daily
  - may be covered with a sterile bandage
- children under 2 years of age: consult a physician

Other information

store at 20°-25°C (68°-77°F)

Inactive ingredients

petrolatum

PRINCIPAL DISPLAY PANEL

Best Choice Antibiotic Ointment Plus Pain Relief